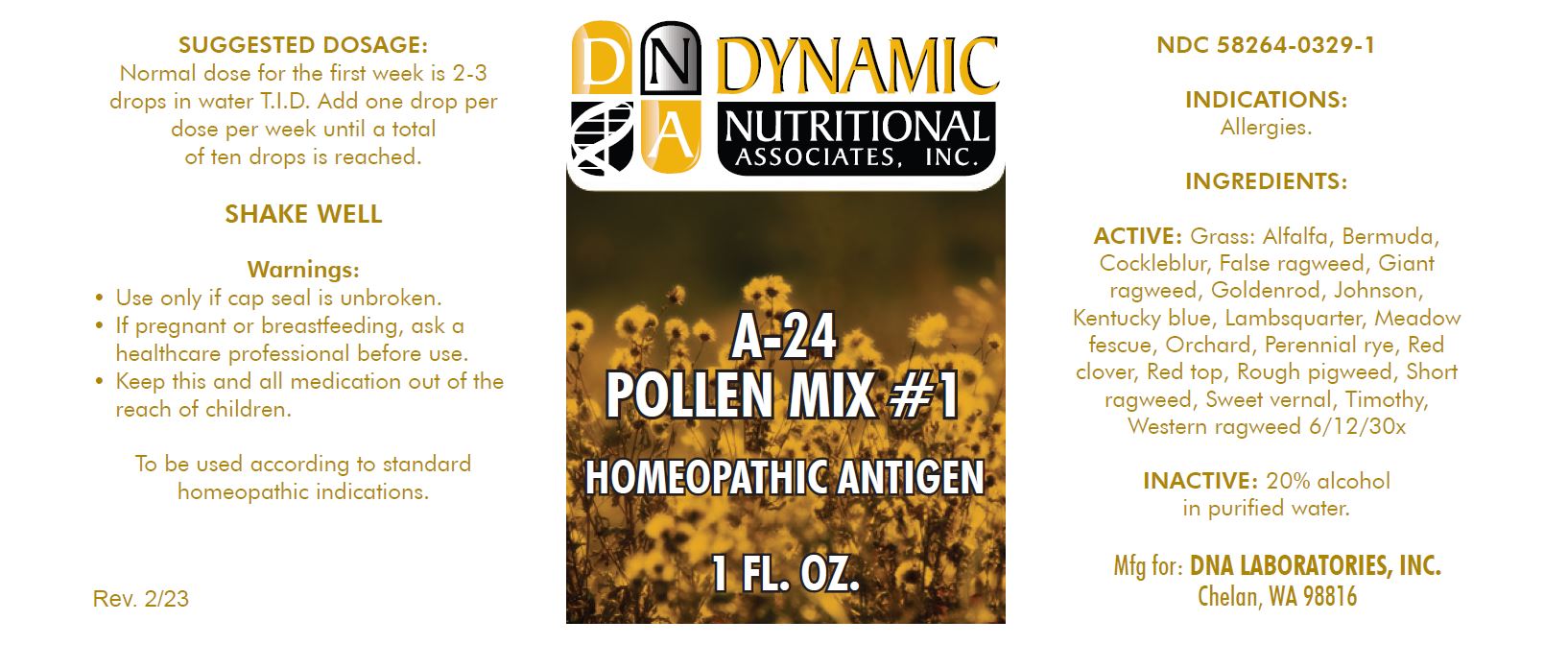 DRUG LABEL: A-24
NDC: 58264-0329 | Form: SOLUTION
Manufacturer: DNA Labs, Inc.
Category: homeopathic | Type: HUMAN OTC DRUG LABEL
Date: 20250109

ACTIVE INGREDIENTS: AGROSTIS GIGANTEA POLLEN 30 [hp_X]/1 mL; FESTUCA PRATENSIS POLLEN 30 [hp_X]/1 mL; POA PRATENSIS POLLEN 30 [hp_X]/1 mL; DACTYLIS GLOMERATA POLLEN 30 [hp_X]/1 mL; PHLEUM PRATENSE POLLEN 30 [hp_X]/1 mL; ANTHOXANTHUM ODORATUM POLLEN 30 [hp_X]/1 mL; LOLIUM PERENNE POLLEN 30 [hp_X]/1 mL; MEDICAGO SATIVA POLLEN 30 [hp_X]/1 mL; TRIFOLIUM PRATENSE POLLEN 30 [hp_X]/1 mL; SOLIDAGO CANADENSIS POLLEN 30 [hp_X]/1 mL; AMBROSIA ACANTHICARPA POLLEN 30 [hp_X]/1 mL; AMBROSIA PSILOSTACHYA POLLEN 30 [hp_X]/1 mL; AMBROSIA TRIFIDA POLLEN 30 [hp_X]/1 mL; AMBROSIA ARTEMISIIFOLIA POLLEN 30 [hp_X]/1 mL; XANTHIUM STRUMARIUM POLLEN 30 [hp_X]/1 mL; CHENOPODIUM ALBUM POLLEN 30 [hp_X]/1 mL; AMARANTHUS RETROFLEXUS POLLEN 30 [hp_X]/1 mL; CYNODON DACTYLON POLLEN 30 [hp_X]/1 mL; SORGHUM HALEPENSE POLLEN 30 [hp_X]/1 mL
INACTIVE INGREDIENTS: ALCOHOL; WATER

A-24

NDC 58264-0329-1

INDICATIONS

PURPOSE

Allergies.

INGREDIENTS

ACTIVE

Grass: Alfalfa, Bermuda, Cockleblur, False ragweed, Giant ragweed, Goldenrod, Johnson, Kentucky blue, Lambsquarter, Meadow fescue, Orchard, Perennial rye, Red clover, Red top, Rough pigweed, Short ragweed, Sweet vernal, Timothy, Western ragweed 6/12/30x

INACTIVE

20% alcohol in purified water.

SUGGESTED DOSAGE

Normal dose for the first week is 2-3 drops in water T.I.D. Add one drop per dose per week until a total of ten drops is reached.

STORAGE AND HANDLING

SHAKE WELL

Warnings

- Use only if cap seal is unbroken.

PREGNANCY OR BREAST FEEDING

- If pregnant or breastfeeding, ask a healthcare professional before use.

KEEP OUT OF REACH OF CHILDREN

- Keep this and all medication out of the reach of children.

To be used according to standard homeopathic indications.

PRINCIPAL DISPLAY PANEL - 1 FL. OZ. Bottle Label

DYNAMIC
NUTRITIONAL
ASSOCIATES, INC.

A-24
POLLEN MIX #1

HOMEOPATHIC ANTIGEN

1 FL. OZ.